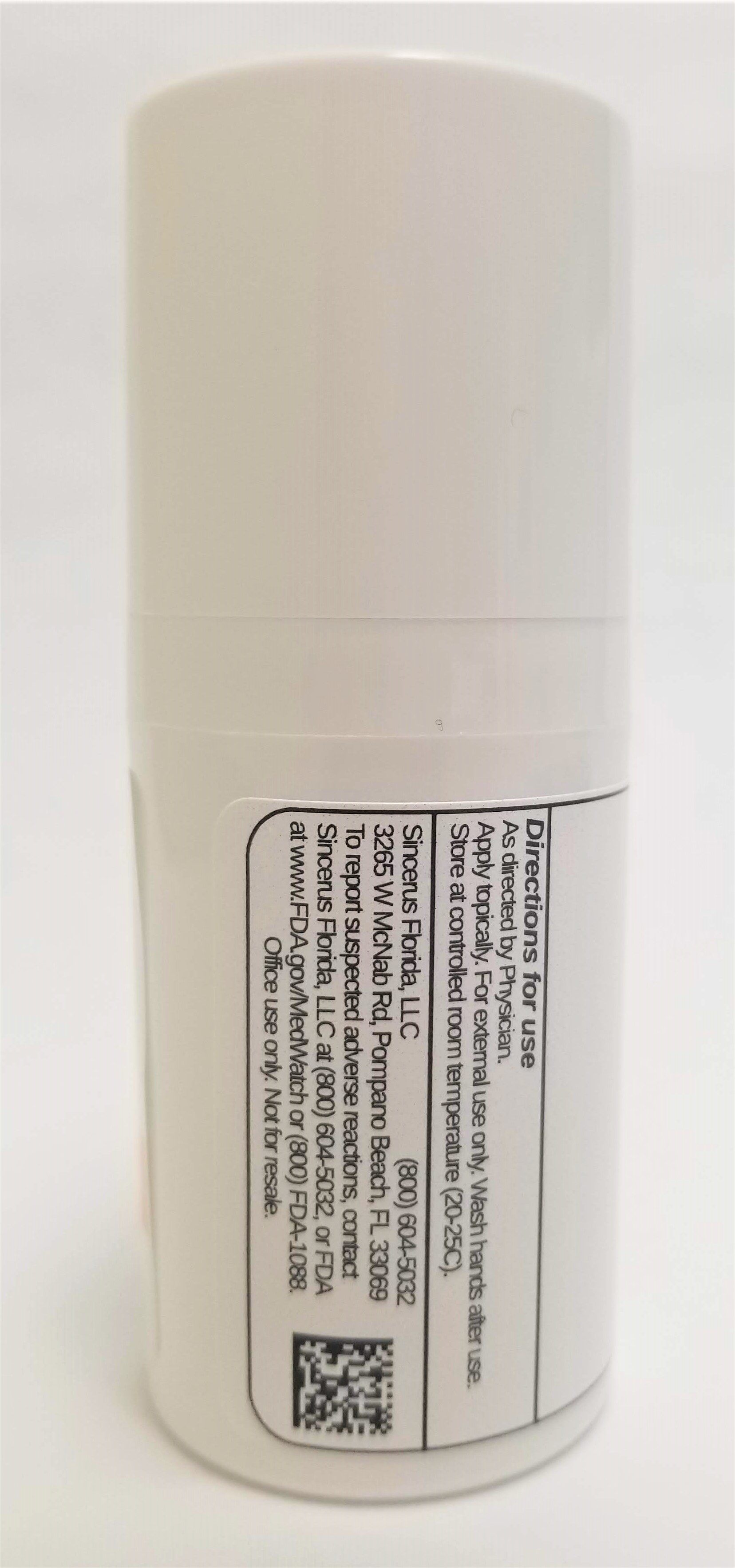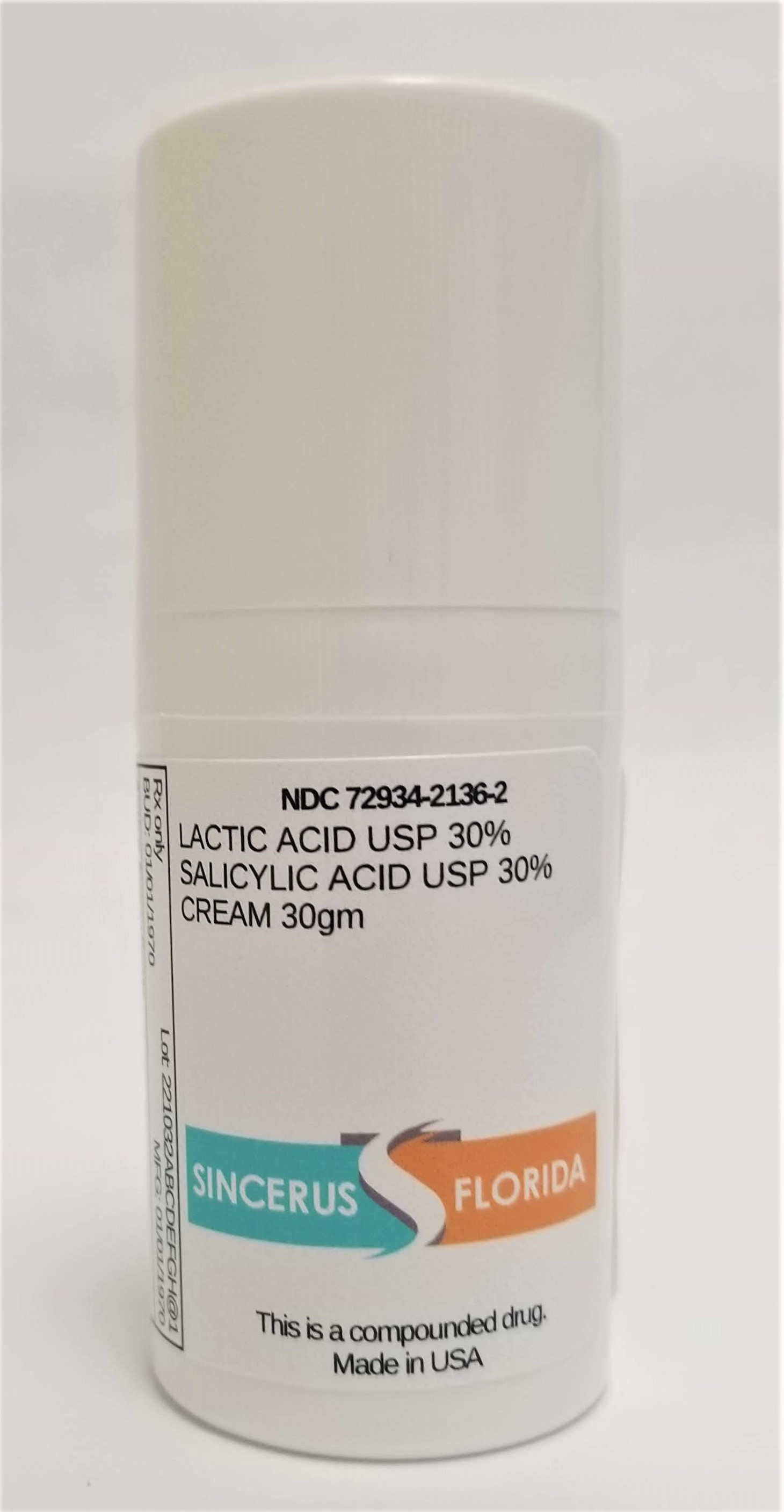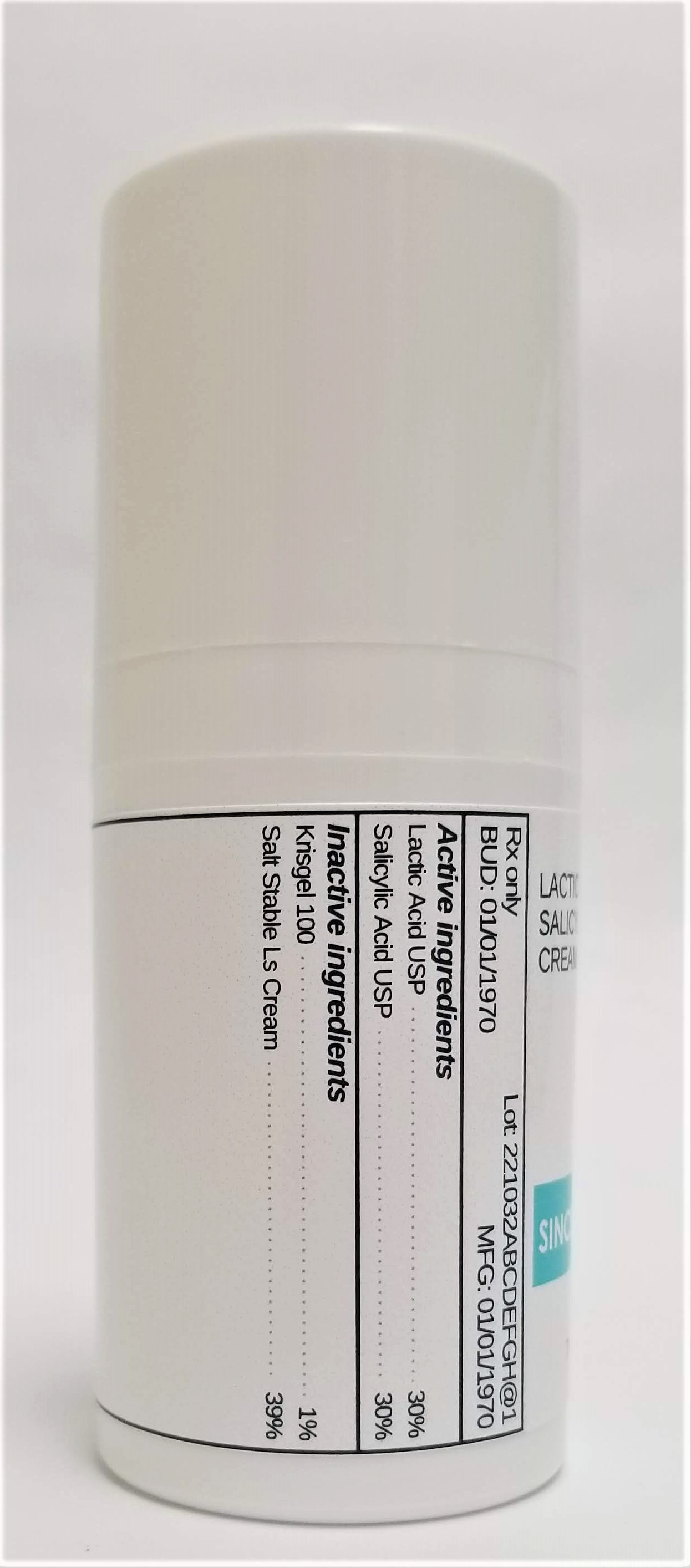 DRUG LABEL: LACTIC ACID 30% / SALICYLIC ACID 30%
NDC: 72934-2136 | Form: CREAM
Manufacturer: Sincerus Florida, LLC
Category: prescription | Type: HUMAN PRESCRIPTION DRUG LABEL
Date: 20190517

ACTIVE INGREDIENTS: SALICYLIC ACID 30 g/100 g; LACTIC ACID 30 g/100 g

LACTIC ACID 30% / SALICYLIC ACID 30%